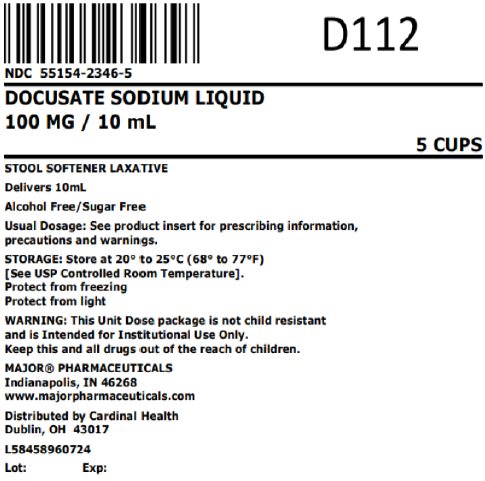 DRUG LABEL: Docusate Sodium
NDC: 55154-2346 | Form: LIQUID
Manufacturer: Cardinal Health 107, LLC
Category: otc | Type: HUMAN OTC DRUG LABEL
Date: 20251002

ACTIVE INGREDIENTS: DOCUSATE SODIUM 50 mg/5 mL
INACTIVE INGREDIENTS: ANHYDROUS CITRIC ACID; D&C RED NO. 33; GLYCERIN; METHYLPARABEN; POLYETHYLENE GLYCOL, UNSPECIFIED; PROPYLENE GLYCOL; PROPYLPARABEN; WATER; SACCHARIN SODIUM; SODIUM CITRATE, UNSPECIFIED FORM; SORBITOL SOLUTION

Docusate Sodium

Active Ingredient

(in each 5 mL)
Docusate sodium 100 mg

Purpose

Stool softener

Uses

- relieves occasional constipation (irregularity)
- generally produces bowel movement in 12 to 72 hours

Warnings

Do not use

- if you are presently taking mineral oil, unless told to do so by a doctor

Ask a doctor before use if you have

- stomach pain
- nausea
- vomiting
- noticed a sudden change in bowel habits that lasts over 2 weeks

Stop use and ask a doctor if

- you have rectal bleeding or fail to have a bowel movement after use of a laxative. These could be signs of a serious condition.
- you need to use a stool softener laxative for more than 1 week
- rash occurs

If pregnant or breast-feeding, ask a health professional before use.

Keep out of reach of children

In case of overdose, get medical help or contact a Poison Control Center right away.

Directions

- Dose once daily
- take with 6 to 8 oz of milk, juice or infant formula to mask the bitter taste.

adults and children 12 years and older | 5 to 20 mL (1 to 4 teaspoonfuls)
children 6 to under 12 years of age | 5 to 10 mL (1 to 2 teaspoonfuls)
children 3 to under 6 years of age | 2.5 to 5 mL (1/2 to 1 teaspoonful)
children under 3 years | ask a doctor

Other information

- Sodium content: 14 mg/5 mL
- Store at controlled room temperature, 20º to 25ºC (68º to 77ºF)
- Protect from freezing
- Protect from light
- Clear pink to purple colored, cherry-vanilla flavored liquid supplied in the following

Overbagged with 5 x 10 mL unit dose cups per bag, NDC 55154-2346-5

WARNING: This Unit Dose package is not child resistant and is Intended for Institutional Use Only. Keep this and all drugs out of the reach of children.

Inactive Ingredients:

artificial cherry vanilla flavoring, citric acid anhydrous, D&C Red No. 33, glycerin, methylparaben, polyethylene glycol, propylene glycol, propylparaben, purified water, saccharin sodium, sodium citrate, and sorbitol

Questions or comments?

Call 1-800-845-8210

Distributed by:

R06/22

MAJOR® PHARMACEUTICALS
Indianapolis, IN 46268

Distributed By:

Cardinal Health

Dublin, OH 43017

L58458960724

Principal Display Panel

NDC 55154-2346-5

DOCUSATE SODIUM LIQUID

100 MG / 10 mL

5 CUPS